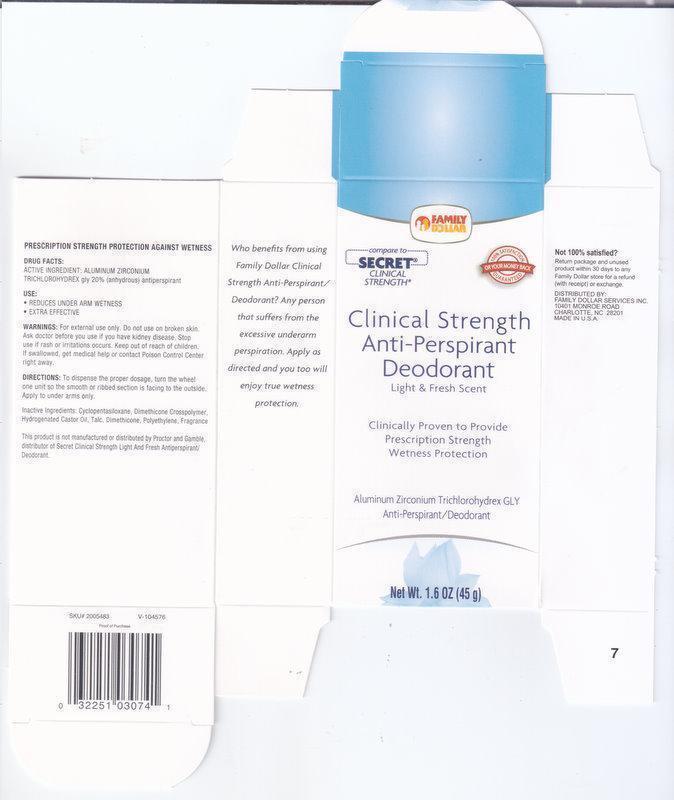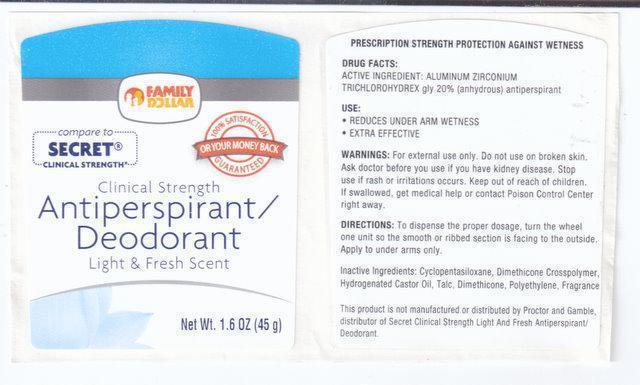 DRUG LABEL: FAMILY DOLLAR
NDC: 55319-013 | Form: STICK
Manufacturer: FAMILY DOLLAR
Category: otc | Type: HUMAN OTC DRUG LABEL
Date: 20130806

ACTIVE INGREDIENTS: ALUMINUM ZIRCONIUM TRICHLOROHYDREX GLY 200 mg/1 g
INACTIVE INGREDIENTS: CYCLOMETHICONE 5; DIMETHICONE; HYDROGENATED CASTOR OIL; TALC; DIMETHICONE/DIENE DIMETHICONE CROSSPOLYMER; HIGH DENSITY POLYETHYLENE

ACTIVE INGREDIENT

Active Ingredients: Aluminum Zirconium Trichlorohydrex Gly 20% (anhydrous)

Purpose: Antiperspirant

Keep out of reach of children.

If swallowed, get medical help or contact a poison control center right away.

Use

- Reduces underarm wetness
- Extra effective

Warning:

For external use only.

Do not use on broken skin.

Ask doctor before you use if you have kidney disease.

Stop use if rash or irritation occurs.

Directions:

To dispense the proper dosage, turn the wheel one unit so the smooth or ribbed section is facing to the outside.Apply to underarms only.

INACTIVE INGREDIENT

Ingredients:Cyclopentasiloxane, Dimethicone crosspolymer, Hydrogenated Castor Oil, Talc, Dimethicone, Polyethylene, Fragrance